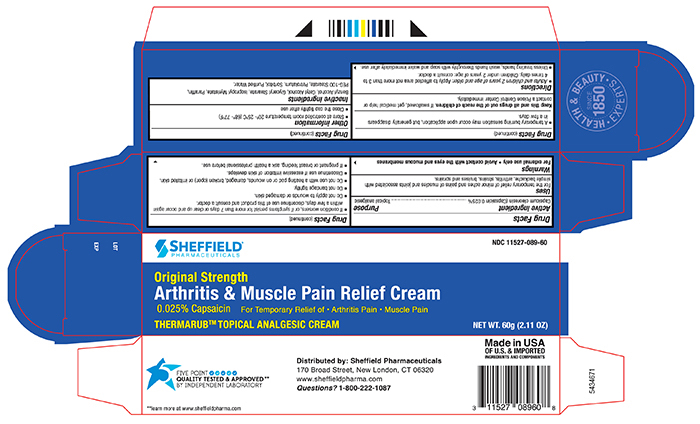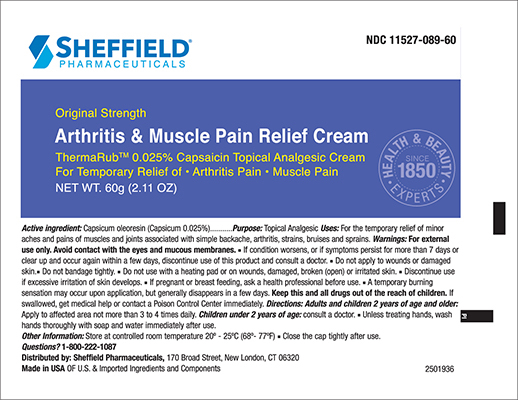 DRUG LABEL: Sheffield Arthritis and Muscle Pain Relief
NDC: 11527-089 | Form: CREAM
Manufacturer: Sheffield Pharmaceuticals LLC
Category: otc | Type: HUMAN OTC DRUG LABEL
Date: 20250922

ACTIVE INGREDIENTS: CAPSICUM OLEORESIN 0.25 mg/1 g
INACTIVE INGREDIENTS: SORBITOL; WATER; ISOPROPYL MYRISTATE; CETYL ALCOHOL; GLYCERYL MONOSTEARATE; PEG-100 STEARATE; BENZYL ALCOHOL; PETROLATUM; PARAFFIN

Sheffield Thermarub Capsaicin Cream

Drug Facts

Active Ingredient

Capsicum Oleoresin 0.025%

Purpose

<Topical analgesic>

Uses

- For the temporary relief of minor aches and pains of muscles and joints associated with simple backache, arthritis,strains,bruises and sprains

Warnings

For external use only
Avoid contact with the eyes and mucous membranes

- If condition worsens, or if symptoms persist for more than 7 days or clear up and occur again within a few days, discontinue use of this product and consult a doctor.
- Do not apply to wounds or damaged skin.
- Do not bandage tightly.
- Do not use with a heating pad or on wounds, damaged, broken (open) or irritated skin.
- Discontinue use if excessive irritation of skin develops.
- If pregnant or breast feeding, ask a health professional before use.
- A temporary burning sensation may occur upon application, but generally disappears in a few days

Keep this and all drugs out of the reach of children.

If swallowed, get medical help or contact a Poison Control Center immediately

Directions

- Adults and children 2 years of age and older: Apply to the affected area not more than 3 to 4 times daily. Children under 2 years of age: consult a doctor.
- Unless treating hands, wash thoroughly with soap and water immediately after use.

Inactive ingredients

Benzyl Alcohol, Cetyl Alcohol, Glyceryl Sterate, Isopropyl Myristate, Paraffin, PEG-100 Stearate, Petrolatum, Purified Water , Sorbitol

Other Information

- Store at controlled room temperature 20°- 25°C (68° - 77°F)
- Close the cap tightly after use

Principal Display Panel – 60 g Carton Label

Sheffield NDC 11527-089-60

Made in the USA

ARTHRITIS & MUSCLE PAIN RELIEF CREAM

Topical Analgesic

NET WT. 60g (2.11oz)

Principal Display Panel – 60g Tube Label

Sheffield NDC 11527-089-60

Made in the USA

ARTHRITIS & MUSCLE PAIN RELIEF CREAM

Topical Analgesic

NET WT. 60g (2.11oz)